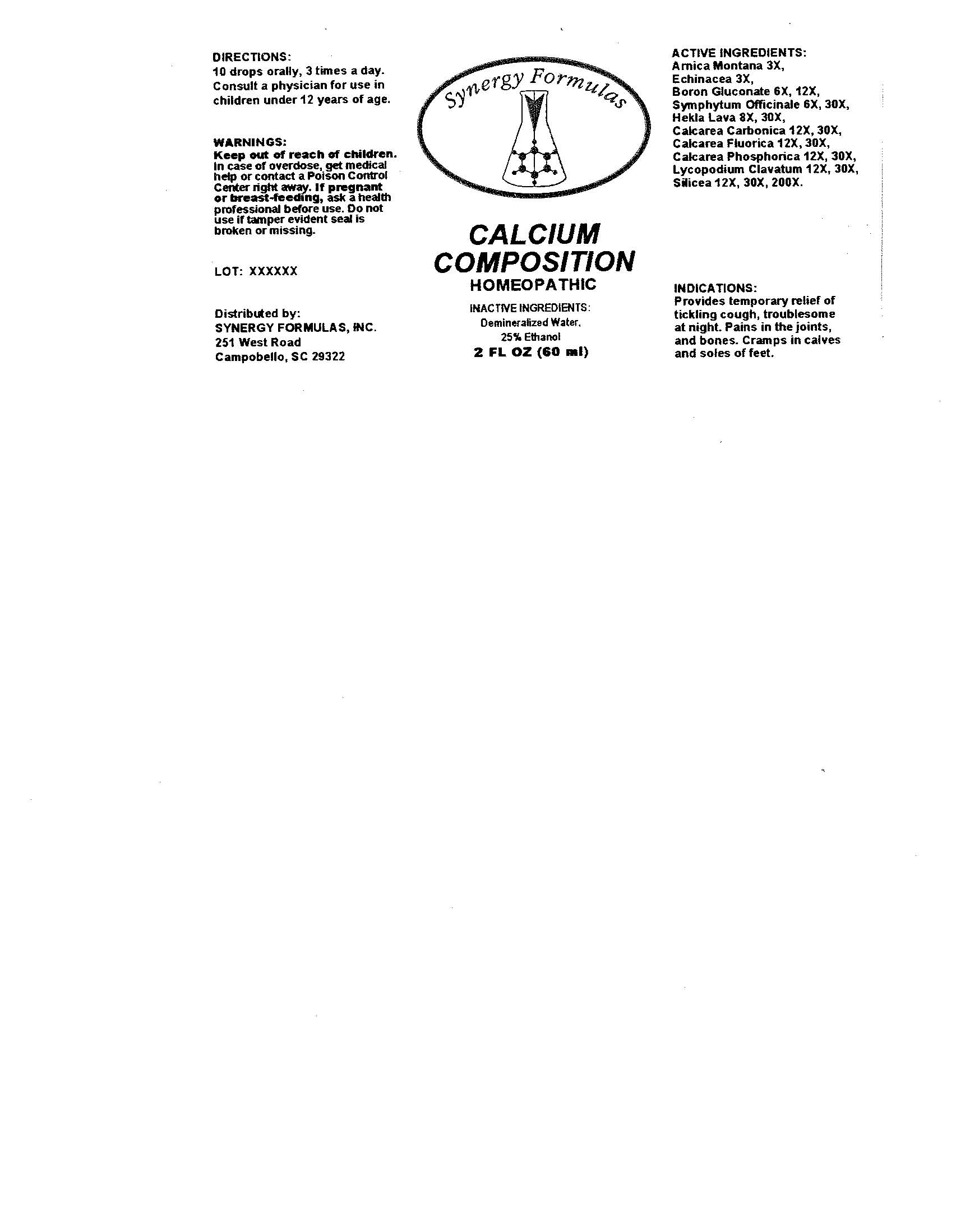 DRUG LABEL: Calcium Composition
NDC: 57520-0320 | Form: LIQUID
Manufacturer: Apotheca Company
Category: homeopathic | Type: HUMAN OTC DRUG LABEL
Date: 20100730

ACTIVE INGREDIENTS: ARNICA MONTANA 3 [hp_X]/1 mL; ECHINACEA 3 [hp_X]/1 mL; COMFREY ROOT 30 [hp_X]/1 mL; HEKLA LAVA 30 [hp_X]/1 mL; OYSTER SHELL CALCIUM CARBONATE, CRUDE 30 [hp_X]/1 mL; CALCIUM FLUORIDE 30 [hp_X]/1 mL; TRIBASIC CALCIUM PHOSPHATE 30 [hp_X]/1 mL; LYCOPODIUM CLAVATUM SPORE 30 [hp_X]/1 mL; SILICON DIOXIDE 200 [hp_X]/1 mL; BORON GLUCONATE 12 [hp_X]/1 mL
INACTIVE INGREDIENTS: WATER; ALCOHOL

Calcium Composition

ACTIVE INGREDIENT

ACTIVE INGREDIENTS: Arnica montana 3X, Echinacea 3X, Boron gluconate 6X, 12X, Symphytum officinale 6X, 30X, Hekla lava 8X, 30X, Calcarea carbonica 12X, 30X, Calcarea fluorica 12X, 30X, Calcarea phosphorica 12X, 30X, Lycopodium clavatum 12X, 30X, Silicea 12X, 30X, 200X.

PURPOSE

INDICATIONS: Provides temporary relief of tickling cough, troublesome at night. Pains in the joints, and bones. Cramps in calves and soles of feet.

WARNINGS

WARNINGS: Keep out of reach of children. In case of overdose, get medical help or contact a Poison Control Center right away.

If pregnant or breast-feeding, ask a health professional before use.
Do not use if tamper evident seal is broken or missing.

DOSAGE AND ADMINISTRATION

DIRECTIONS: 10 drops orally, 3 times a day. Consult a physician for use in children under 12 years of age.

INACTIVE INGREDIENTS: Demineralized water, 25% Ethanol

QUESTIONS

Distributed By:

SYNERGY FORMULAS, INC.

251 West Road

Campobello SC 29322

PACKAGE LABEL

Synergy Formulas

CALCIUM COMPOSITION

HOMEOPATHIC

2 FL OZ (30 ML)